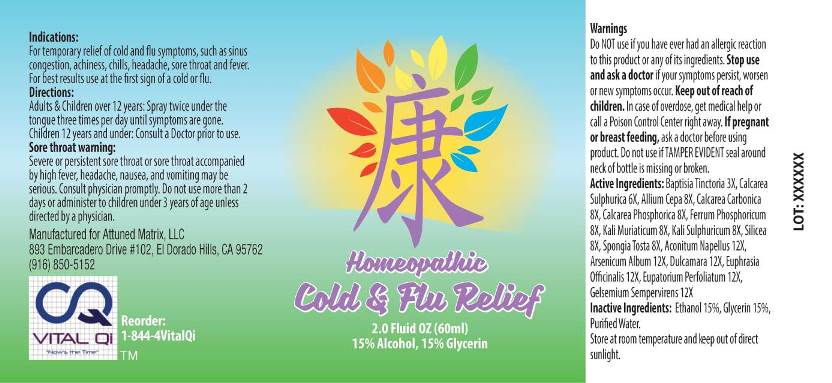 DRUG LABEL: Cold and Flu Relief
NDC: 71144-0001 | Form: SPRAY
Manufacturer: Attuned Matrix, LLC
Category: homeopathic | Type: HUMAN OTC DRUG LABEL
Date: 20170616

ACTIVE INGREDIENTS: BAPTISIA TINCTORIA ROOT 3 [hp_X]/1 mL; CALCIUM SULFATE ANHYDROUS 6 [hp_X]/1 mL; ONION 8 [hp_X]/1 mL; OYSTER SHELL CALCIUM CARBONATE, CRUDE 8 [hp_X]/1 mL; TRIBASIC CALCIUM PHOSPHATE 8 [hp_X]/1 mL; FERRUM PHOSPHORICUM 8 [hp_X]/1 mL; POTASSIUM CHLORIDE 8 [hp_X]/1 mL; POTASSIUM SULFATE 8 [hp_X]/1 mL; SILICON DIOXIDE 8 [hp_X]/1 mL; SPONGIA OFFICINALIS SKELETON, ROASTED 8 [hp_X]/1 mL; ACONITUM NAPELLUS 12 [hp_X]/1 mL; ARSENIC TRIOXIDE 12 [hp_X]/1 mL; SOLANUM DULCAMARA TOP 12 [hp_X]/1 mL; EUPHRASIA STRICTA 12 [hp_X]/1 mL; EUPATORIUM PERFOLIATUM FLOWERING TOP 12 [hp_X]/1 mL; GELSEMIUM SEMPERVIRENS ROOT 12 [hp_X]/1 mL
INACTIVE INGREDIENTS: WATER; ALCOHOL; GLYCERIN

Drug Facts:

ACTIVE INGREDIENTS:

Baptisia Tinctoria 3X, Calcarea Sulphurica 6X, Allium Cepa 8X, Calcarea Carbonica 8X, Calcarea Phosphorica 8X, Ferrum Phosphoricum 8X, Kali Muriaticum 8X, Kali Sulphuricum 8X, Silicea 8X, Spongia Tosta 8X, Aconitum Napellus 12X, Arsenicum Album 12X, Dulcamara 12X, Euphrasia Officinalis 12X, Eupatorium Perfoliatum 12X, Gelsemium Sempervirens 12X

INDICATIONS:

For temporary relief of cold and flu symptoms, such as sinus congestion, achiness, chills, headache, sore throat and fever. For best results use at the first sign of a cold or flu.

WARNINGS:

Do NOT use if you have ever had an allergic reaction to this product or any of its ingredients.

Stop use and ask a doctor if your symptoms persist, worsen or new symptoms occur.

Keep out of reach of children. In case of overdose, get medical help or call a Poison Control Center right away.

If pregnant or breast feeding, ask a doctor before using product.

Do not use if TAMPER EVIDENT seal around neck of bottle is missing or broken

Store at room temperature and keep out of direct sunlight.

Keep out of reach of children. In case of overdose, get medical help or call a Poison Control Center right away.

DIRECTIONS:

Adults & children over 12 years: Spray twice under the tongue three times per day until symptoms are gone.

Children 12 years and under: Consult a Doctor prior to use.

Sore Throat Warning:

Severe or persistent sore throat or sore throat accompanied by high fever, headache, nausea, and vomiting may be serious. Consult physician promptly. Do not use more than 2 days or administer to children under 3 years of age unless directed by a physician.

INDICATIONS:

For temporary relief of cold and flu symptoms, such as sinus congestion, achiness, chills, headache, sore throat and fever. For best results use at the first sign of a cold or flu.

INACTIVE INGREDIENTS:

Ethanol 15%, Glycerin 15%, Purified Water.

QUESTIONS:

Manufactured for Attuned Matrix, LLC

893 Embarcadero Drive #102, El Dorado Hills, CA 95762

(916) 850-5152

PACKAGE LABEL DISPLAY:

Homeopathic

Cold & Flu Relief

2.0 Fluid OZ (60ml)